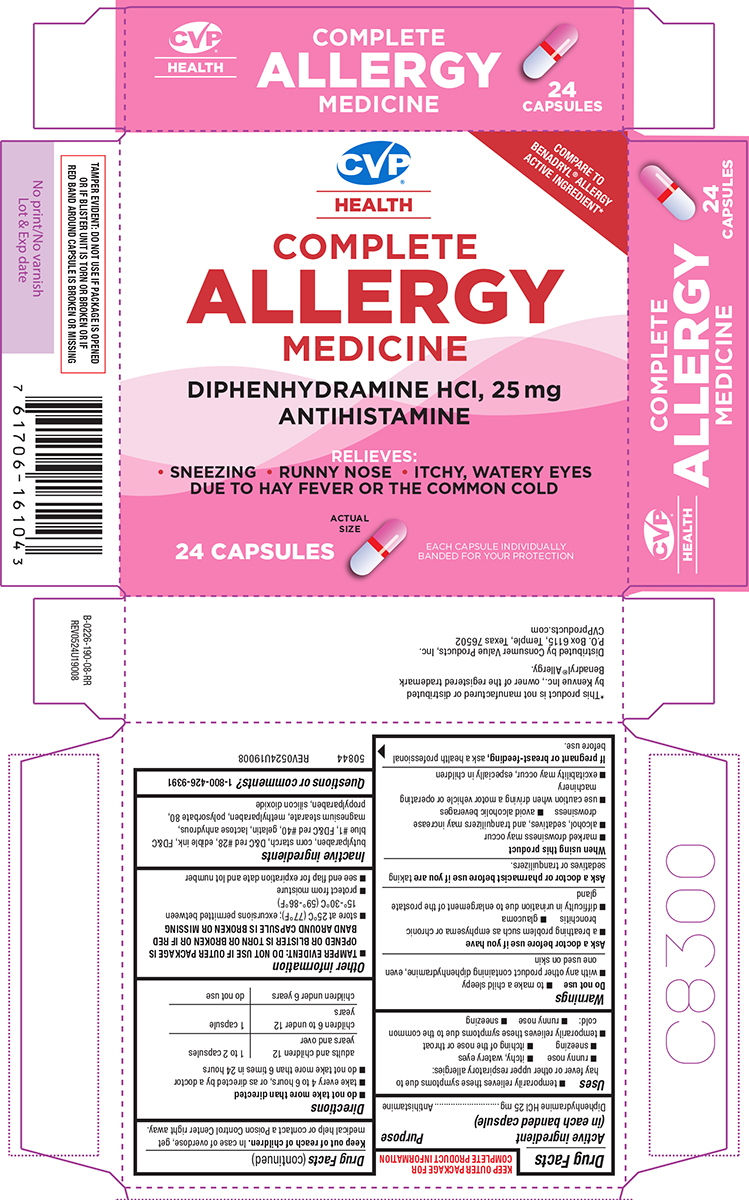 DRUG LABEL: Complete Allergy Medicine
NDC: 57243-190 | Form: CAPSULE
Manufacturer: Salado Sales, Inc.
Category: otc | Type: HUMAN OTC DRUG LABEL
Date: 20260106

ACTIVE INGREDIENTS: DIPHENHYDRAMINE HYDROCHLORIDE 25 mg/1 1
INACTIVE INGREDIENTS: BUTYLPARABEN; STARCH, CORN; D&C RED NO. 28; FD&C BLUE NO. 1; FD&C RED NO. 40; GELATIN, UNSPECIFIED; ANHYDROUS LACTOSE; MAGNESIUM STEARATE; METHYLPARABEN; POLYSORBATE 80; PROPYLPARABEN; SILICON DIOXIDE

CVP 44-190

Active ingredient (in each banded capsule)

Diphenhydramine HCl 25 mg

Purpose

Antihistamine

Uses

- temporarily relieves these symptoms due to hay fever or other upper respiratory allergies:
  - runny nose
  - itchy, watery eyes
  - sneezing
  - itching of the nose or throat
- temporarily relieves these symptoms due to the common cold:
  - runny nose
  - sneezing

Warnings

Do not use

- to make a child sleepy
- with any other product containing diphenhydramine, even one used on skin

Ask a doctor before use if you have

- a breathing problem such as emphysema or chronic bronchitis
- glaucoma
- difficulty in urination due to enlargement of the prostate gland

Ask a doctor or pharmacist before use if you are

taking sedatives or tranquilizers.

When using this product

- marked drowsiness may occur
- avoid alcoholic beverages
- alcohol, sedatives, and tranquilizers may increase drowsiness
- use caution when driving a motor vehicle or operating machinery
- excitability may occur, especially in children

If pregnant or breast-feeding,

ask a health professional before use.

Keep out of reach of children.

In case of overdose, get medical help or contact a Poison Control Center right away.

Directions

- do not take more than directed
- take every 4 to 6 hours, or as directed by a doctor
- do not take more than 6 times in 24 hours

adults and children 12 years and over | 1 to 2 capsules
children 6 to under 12 years | 1 capsule
children under 6 years | do not use

Other information

- TAMPER EVIDENT: DO NOT USE IF OUTER PACKAGE IS OPENED OR BLISTER IS TORN OR BROKEN OR IF RED BAND AROUND CAPSULE IS BROKEN OR MISSING
- store at 25°C (77°F); excursions permitted between 15°-30°C (59°-86°F)
- protect from moisture
- see end flap for expiration date and lot number

Inactive ingredients

butylparaben, corn starch, D&C red #28, edible ink, FD&C blue #1, FD&C red #40, gelatin, lactose anhydrous, magnesium stearate, methylparaben, polysorbate 80, propylparaben, silicon dioxide

Questions or comments?

1-800-426-9391

Principal Display Panel

COMPARE TO
BENADRYL® ALLERGY
ACTIVE INGREDIENT*

CVP®
HEALTH

COMPLETE
ALLERGY
MEDICINE

DIPHENHYDRAMINE HCl, 25 mg
ANTIHISTAMINE

RELIEVES:
• SNEEZING • RUNNY NOSE • ITCHY, WATERY EYES
DUE TO HAY FEVER OR THE COMMON COLD

24 CAPSULES

ACTUAL
SIZE

EACH CAPSULE INDIVIDUALLY
BANDED FOR YOUR PROTECTION

TAMPER EVIDENT: DO NOT USE IF PACKAGE IS OPENED
OR IF BLISTER UNIT IS TORN OR BROKEN OR IF
RED BAND AROUND CAPSULE IS BROKEN OR MISSING

50844 REV0524U19008

This product is not manufactured or distributed
by Kenvue Inc., owner of the registered trademark
Benadryl® Allergy.

Distributed by Consumer Value Products, Inc.
P.O. Box 6115, Temple, Texas 76502
CVPproducts.com

CVP 44-190